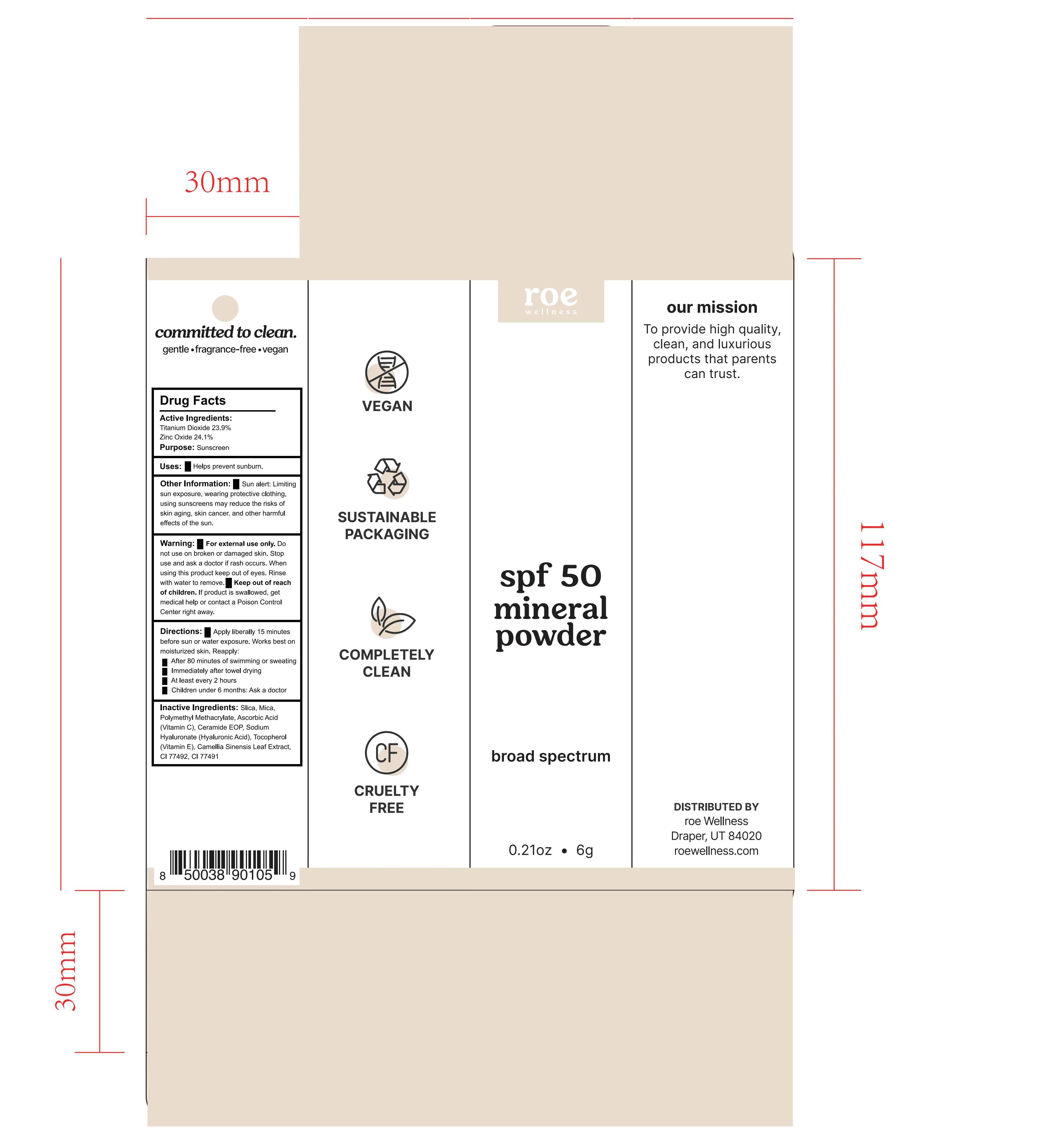 DRUG LABEL: ROE WELLNESS SPF 50 MINERAL
NDC: 87283-003 | Form: POWDER
Manufacturer: Aopline Biotechnology (Guangzhou) Co., Ltd.
Category: otc | Type: HUMAN OTC DRUG LABEL
Date: 20260108

ACTIVE INGREDIENTS: ZINC OXIDE 24.1 g/100 g; TITANIUM DIOXIDE 23.9 g/100 g
INACTIVE INGREDIENTS: CI 77492; ASCORBIC ACID; CI 77491; MICA; POLY(METHYL METHACRYLATE; 450000 MW); .ALPHA.-TOCOPHEROL; CAMELLIA SINENSIS LEAF; SILICA; CERAMIDE 9; HYALURONATE SODIUM

87283-003-01 ROE wellness spf 50 mineral powder

ACTIVE INGREDIENT

Titanium Dioxide 23.9%
Zinc Oxide 24.1%

Keep out of reach of children . If product is swallowed , get medical help or contact a Poison Control Center right away .

PURPOSE

Uses: Helps prevent sunburn.

WARNINGS

For external use only .
Do not use on broken or damaged skin .
Stop use and ask a doctor if rash occurs
When using this product keep out of eyes . Rinse with water to remove .
Keep out of reach of children . If product is swallowed , get medical help or contact a Poison Control Center right away .

DOSAGE AND ADMINISTRATION

Immediately after towel drying.
At least every 2 hours.

INDICATIONS AND USAGE

Directions : Apply liberally 15 minutes before sun or water exposure. Works best on moisturized skin.
Reapply:
After 80 minutes of swimming or sweating.
Immediately after towel drying.
At least every 2 hours.
Children under 6 months: Ask a doctor.

INACTIVE INGREDIENT

Slica , Mica, Polymethyl Methacrylate, Ascorbic Acid (Vitamin C), Ceramide EOP, Sodium Hyaluronate (Hyaluronic Acid), Tocopherol Vitamin E), Camellia Sinensis Leaf Extract, CI 77492, CI 77491